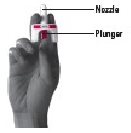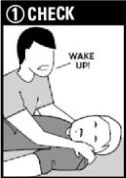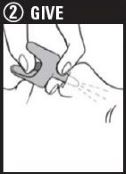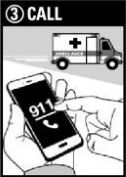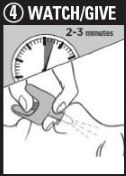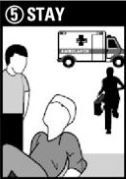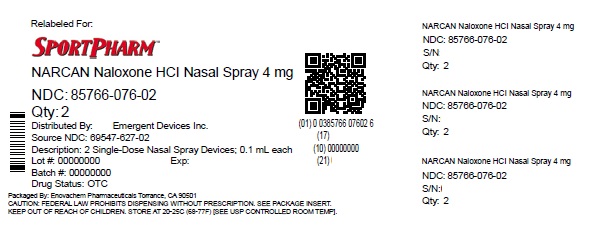 DRUG LABEL: NARCAN
NDC: 85766-076 | Form: SPRAY
Manufacturer: Sportpharm, Inc. dba Sportpharm
Category: otc | Type: HUMAN OTC DRUG LABEL
Date: 20251010

ACTIVE INGREDIENTS: NALOXONE HYDROCHLORIDE 4 mg/0.1 mL
INACTIVE INGREDIENTS: BENZALKONIUM CHLORIDE; EDETATE DISODIUM; SODIUM CHLORIDE; WATER; HYDROCHLORIC ACID

NARCAN® Naloxone HCl Nasal Spray 4 mg Drug Facts

Active ingredient (in each spray)

Naloxone Hydrochloride 4 mg

Purpose

Emergency treatment of opioid overdose

Uses

- to “revive” someone during an overdose from many prescription pain medicationsor street drugs such as heroin
- this medicine can save a life

Warning

- When using this productsome people may experience symptoms when they wake up, such as, shaking, sweating, nausea, or feeling angry. This is to be expected.

KEEP OUT OF REACH OF CHILDREN

Directions

NARCAN®
Naloxone HCl Nasal Spray 4 mg

Emergency Treatment of Opioid Overdose

Important:

- For use in the nose only
- Do not test nasal spray device before use
- 1 nasal spray device contains 1 dose of medicine
- Each device sprays 1 time only

Step 1: CHECK if you suspect an overdose:

- CHECKfor a suspected overdose:the person will not wake up or is very sleepy or not breathing well
  - yell “Wake up!”
  - shake the person gently
  - if the person is not awake, go to Step 2

Step 2: Give 1st dose in the nose

- HOLDthe nasal spray device with your thumb on the bottom of the plunger
- INSERTthe nozzle into either NOSTRIL
- PRESSthe plunger firmly to give the 1st dose
- 1 nasal spray device contains 1 dose

Step 3: CALL 911

- CALL 911immediately after giving the lstdose

Step 4: WATCH & GIVE

- WAIT2-3 minutes after the lstdose to give the medicine time to work
- if the person wakes up: Go to Step 5
- if the person does not wake up:
  - CONTINUE TO GIVEdoses every 2-3 minutes until the person wakes up
  - it is safe to keep giving doses

Step 5: STAY

- STAYuntil ambulance arrives: even if the person wakes up
- GIVEanother dose if the person becomes very sleepy again
- You may need to give all the doses in the pack

For opioid emergencies, call 911.For questions on NARCAN, call 1-844-4NARCAN (1-844-462-7226) or go to www.narcan.com.

©2023 Emergent Devices Inc. EMERGENT® and NARCAN® are registered trademarks of Emergent BioSolutions Inc, or its subsidiaries.

Other Information

- store at room temperature or refrigerated, between 2°C to 25°C (36°F to 77°F)
- do not freeze
- avoid excessive heat above 40°C (104°F)
- protect from light
- the product is packaged in individually-sealed blisters.
  Do not use if the blister is open or torn, or if the device appears damaged.

Inactive Ingredients

benzalkonium chloride, edetate disodium, hydrochloric acid, sodium chloride, water

Questions?

Call 1-844-4NARCAN (1-844-462-7226) or go to www.narcan.com